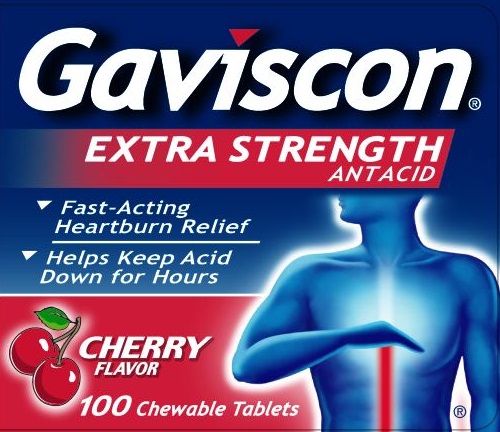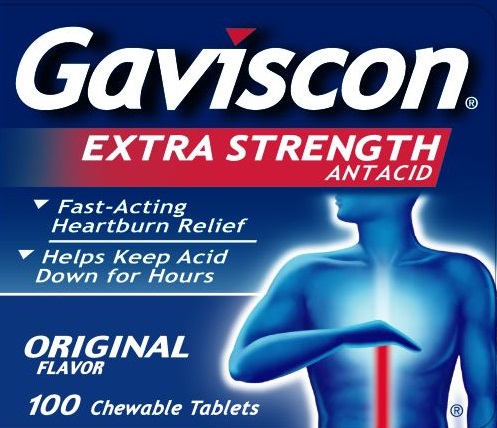 DRUG LABEL: Gaviscon
NDC: 0135-0098 | Form: TABLET, CHEWABLE
Manufacturer: Haleon US Holdings LLC
Category: otc | Type: HUMAN OTC DRUG LABEL
Date: 20250611

ACTIVE INGREDIENTS: ALUMINUM HYDROXIDE 160 mg/1 1; MAGNESIUM CARBONATE 105 mg/1 1
INACTIVE INGREDIENTS: ALGINIC ACID; CALCIUM STEARATE; SODIUM BICARBONATE; SUCROSE; STEARIC ACID; SORBITOL; MANNITOL; STARCH, CORN

Drug Facts

Active ingredients (in each tablet)

Aluminum hydroxide 160mg

Magnesium carbonate 105mg

Purpose

Antacid

Antacid

Uses

relieves

- acid indigestion
- heartburn
- sour stomach
- upset stomach associated with these symptoms

Warnings

Ask a doctor or pharmacist before use if you are

- taking a prescription drug. Antacids may interact with certain prescription drugs.
- if you are on a sodium-restricted diet

When using this product

- do not take more than 16 tablets in 24 hours
- do not use the maximum dosage for more than 2 weeks

Keep out of reach of children.

In case of overdose, get medical help or contact a Poison Control Center right away.

Directions

- chew 2-4 tablets four times a day or as directed by a doctor
- take after meals and at bedtime or as needed
- for best results follow by a half glass of water or other liquid
- DO NOT SWALLOW WHOLE

Other information

- Each tablet contains: magnesium 35mg, sodium 20mg
- Store at up to 25°C (77°F) in a dry place

Inactive ingredients (Extra Strength)

alginic acid, calcium stearate, flavor, sodium bicarbonate, and sucrose. May contain stearic acid. Contains sorbitol or mannitol. May contain starch.

Inactive ingredients (Extra Strength Cherry)

acesulfame k, alginic acid, artificial flavor, calcium stearate, corn starch, corn syrup solids, mannitol, sodium bicarbonate, stearic acid, sucrose

Questions or comments?

call toll-free 1-800-452-0051 (English/Spanish) weekdays

Generic Section

IMPORTANT: Do not use if foil inner seal printed “SEALED for YOUR PROTECTION” is disturbed or missing.

Principal Display Panel (Extra Strength Original Flavor)

Gaviscon®

EXTRA STRENGTH

ANTACID

- Fast-Acting Heartburn Relief
- Helps Keep Acid Down for Hours

ORIGINAL FLAVOR

100 Chewable Tablets

Trademarks owned or licensed by Haleon.

Distributed by:

Haleon, Warren, NJ 07059

Made in France

©2024 Haleon or licensor.

215894 – Bottle Label

Principal Display Panel (Extra Strength Cherry Flavor)

Gaviscon®

EXTRA STRENGTH

ANTACID

- Fast-Acting Heartburn Relief
- Helps Keep Acid Down for Hours

CHERRY FLAVOR

100 Chewable Tablets